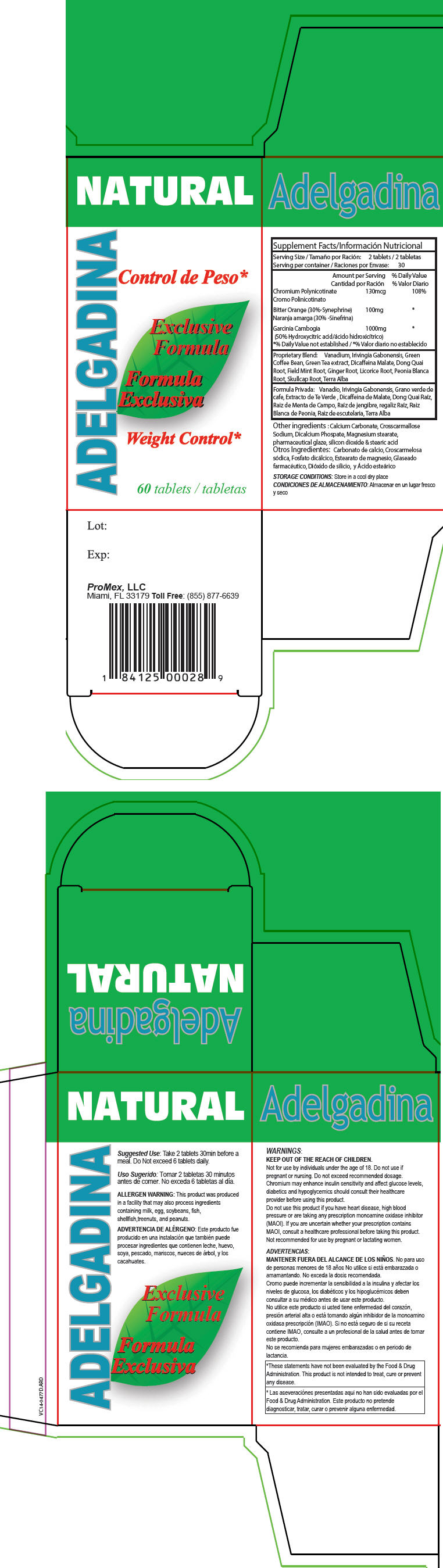 DRUG LABEL: ADELGADINA
NDC: 58988-1820 | Form: TABLET
Manufacturer: ProMex LLC
Category: other | Type: DIETARY SUPPLEMENT
Date: 20151123

ACTIVE INGREDIENTS: CHROMIUM NICOTINATE 130 ug/1 1; CITRUS AURANTIUM FRUIT 100 mg/1 1; GARCINIA GUMMI-GUTTA FRUIT 1000 mg/1 1
INACTIVE INGREDIENTS: VANADIUM; BUSH MANGO; ARABICA COFFEE BEAN; GREEN TEA LEAF; CAFFEINE; ANGELICA SINENSIS ROOT; MENTHA ARVENSIS WHOLE; GINGER; LICORICE; PAEONIA LACTIFLORA ROOT; SCUTELLARIA LATERIFLORA; CALCIUM SULFATE DIHYDRATE; CALCIUM CARBONATE; CROSCARMELLOSE SODIUM; ANHYDROUS DIBASIC CALCIUM PHOSPHATE; MAGNESIUM STEARATE; SHELLAC; SILICON DIOXIDE; STEARIC ACID

ADELGADINA

STATEMENT OF IDENTITY

Supplement Facts

Serving Size: 2 tablets

Serving per container: 30

Amount per Serving

% Daily Value

Chromium Polynicotinate

130mcg

108%

Bitter Orange (30%-Synephrine)

100mg

[% Daily Value not established]

Garcinia Cambogia
(50% Hydroxycitric acid)

1000mg

Proprietary Blend: Vanadium, Irivingia Gabonensis, Green Coffee Bean, Green Tea extract, Dicaffeina Malate, Dong Quai Root, Field Mint Root, Ginger Root, Licorice Root, Peonia Blanca Root, Skullcap Root, Terra Alba

Other ingredients : Calcium Carbonate, Crosscarmallose Sodium, Dicalcium Phospate, Magnesium stearate, pharmaceutical glaze, silicon dioxide & stearic acid

STORAGE CONDITIONS

Store in a cool dry place

Suggested Use

Take 2 tablets 30min before a meal. Do Not exceed 6 tablets daily.

ALLERGEN WARNING

This product was produced in a facility that may also process ingredients containing milk, egg, soybeans, fish, shellfish,treenuts, and peanuts.

WARNINGS

KEEP OUT OF THE REACH OF CHILDREN.

Not for use by individuals under the age of 18. Do not use if pregnant or nursing. Do not exceed recommended dosage. Chromium may enhance insulin sensitivity and affect glucose levels, diabetics and hypoglycemics should consult their healthcare provider before using this product.

Do not use this product if you have heart disease, high blood pressure or are taking any prescription monoamine oxidase inhibitor (MAOI). If you are uncertain whether your prescription contains MAOI, consult a healthcare professional before taking this product. Not recommended for use by pregnant or lactating women.

*These statements have not been evaluated by the Food & Drug Administration. This product is not intended to treat, cure or prevent any disease.

HEALTH CLAIM

Lot:

Exp:

ProMex, LLC
Miami, FL 33179 Toll Free: (855) 877-6639

PRINCIPAL DISPLAY PANEL - 60 Tablet Bottle Box

NATURAL

ADELGADINA

Exclusive
Formula

Weight Control*

60 tablets